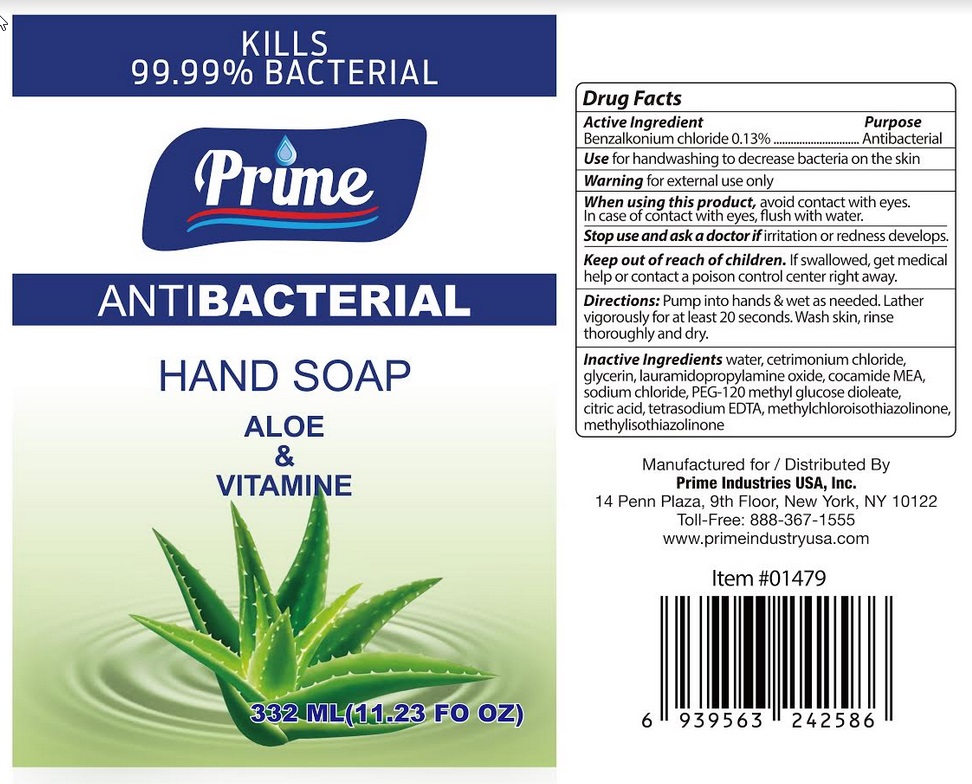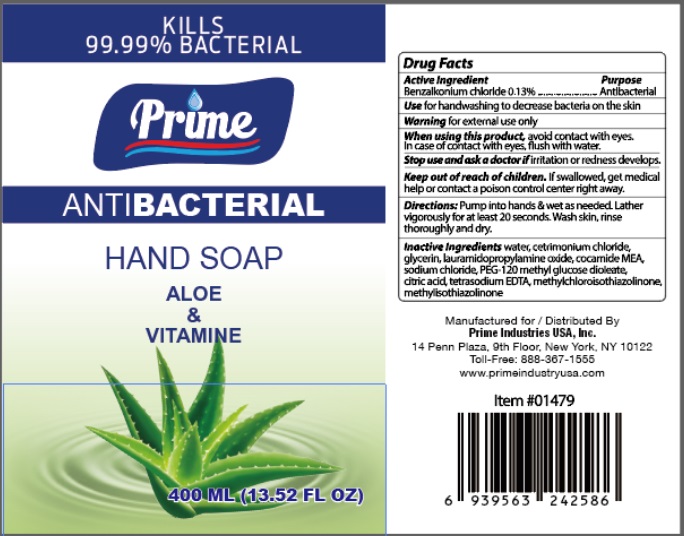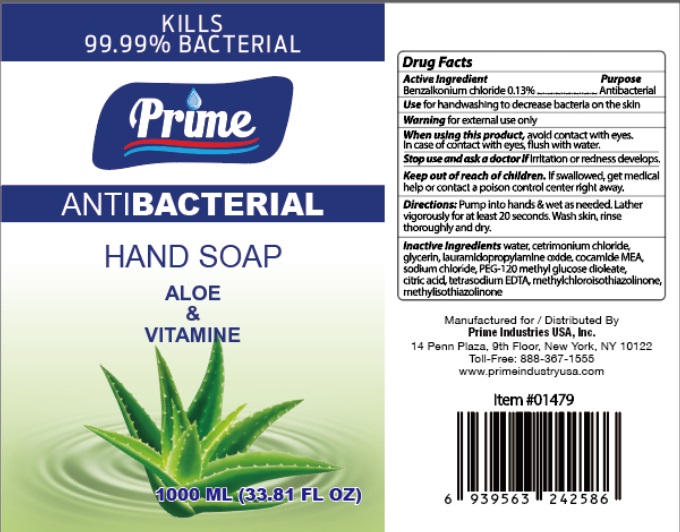 DRUG LABEL: Prime
NDC: 79382-002 | Form: SOAP
Manufacturer: Prime Industries Usa, Inc
Category: otc | Type: HUMAN OTC DRUG LABEL
Date: 20200804

ACTIVE INGREDIENTS: BENZALKONIUM CHLORIDE 1.3 mg/1 mL
INACTIVE INGREDIENTS: WATER; CETRIMONIUM CHLORIDE; GLYCERIN; LAURAMIDOPROPYLAMINE OXIDE; COCAMIDOPROPYL BETAINE; SODIUM CHLORIDE; PEG-120 METHYL GLUCOSE DIOLEATE; CITRIC ACID MONOHYDRATE; EDETATE SODIUM TETRAHYDRATE; METHYLCHLOROISOTHIAZOLINONE; METHYLISOTHIAZOLINONE

Active Ingredient

Benzalkonium chloride 0.13% w/v

Purpose

Antibacterial

Use

For handwashing to decrease bacteria on the skin

Warnings

For external use only

When using this product, avoid contact with eyes. In case of contact with eyes, flush with water.

Stop use and ask a doctor if irritation or redness develops.

Keep out of reach of children. If swallowed, get medical help or contact a Poison Control Center right away.

Directions

Pump into hands & wet as needed. Lather vigorously for at least 20 seconds. Wash skin, rinse thoroughly and dry

Inactive ingredients

Water, cetrimonium chloride, glycerin, lauramidopropylamine oxide, cocamide MEA, sodium chloride, PEG-120 methyl glucose dioleate, citric acid, tetrasodium EDTA, methylchloroisothiazolinone, methylisothiazolinone.